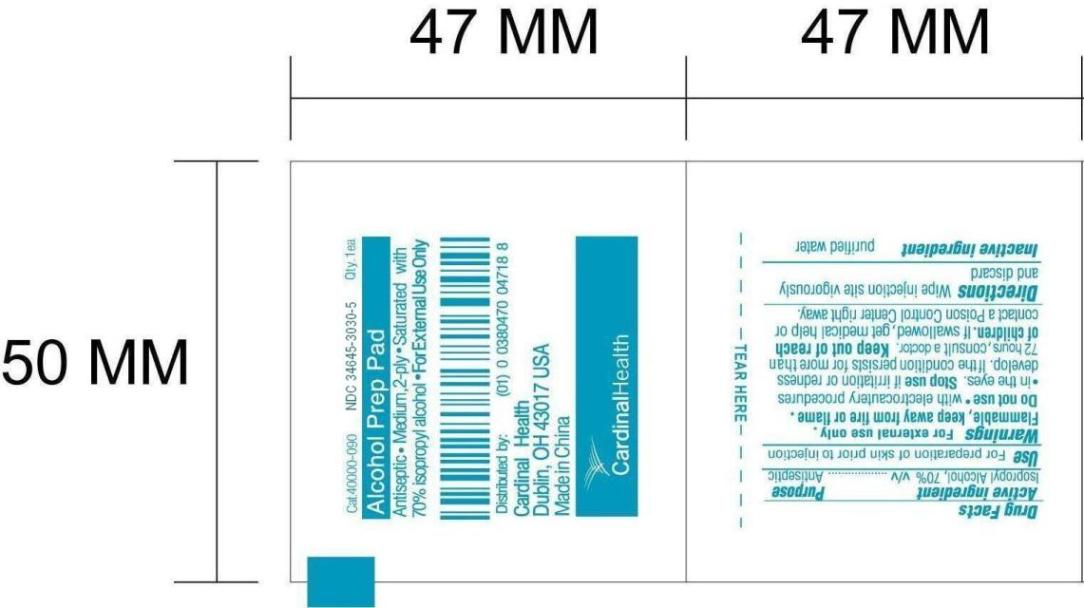 DRUG LABEL: Alcohol Prep Pad
NDC: 34645-3030 | Form: SWAB
Manufacturer: Jiangsu Province JianErKang Medical Dressing Co. ,Ltd.
Category: otc | Type: HUMAN OTC DRUG LABEL
Date: 20100101

ACTIVE INGREDIENTS: ISOPROPYL ALCOHOL 0.7 mL/1 mL
INACTIVE INGREDIENTS: Water 0.3 mL/1 mL

Drug Facts

PACKAGE LABEL

Cat. 40000-090 NDC 34645-3030-5 Qty.1ea
Alcohol Prep Pad
Antiseptic * Medium, 2-ply * Saturated with 70% isopropyl alcohol * For External Use Only
Distributed by:
Cardinal Health
Dublin, OH 43017 USA
Made in China

Active ingredient
Isopropyl Alcohol, 70% v/v

Purpose
Antiseptic

Use
For preparation of skin prior to injection

Warnings
For external use only.
Flammable, keep away from fire or flame.

Do not use
with electrocautery procedures, in the eyes.

Stop use
if irritation or redness develop. If the condition persists for more than 72 hours, consult a doctor.

Keep out of reach of children.
If swallowed, get medical help or contact a Poison Control Center right way.

Directions
Wipe injection site vigorously and discard

Inactive ingredient
purified water

Image of Pouch Label